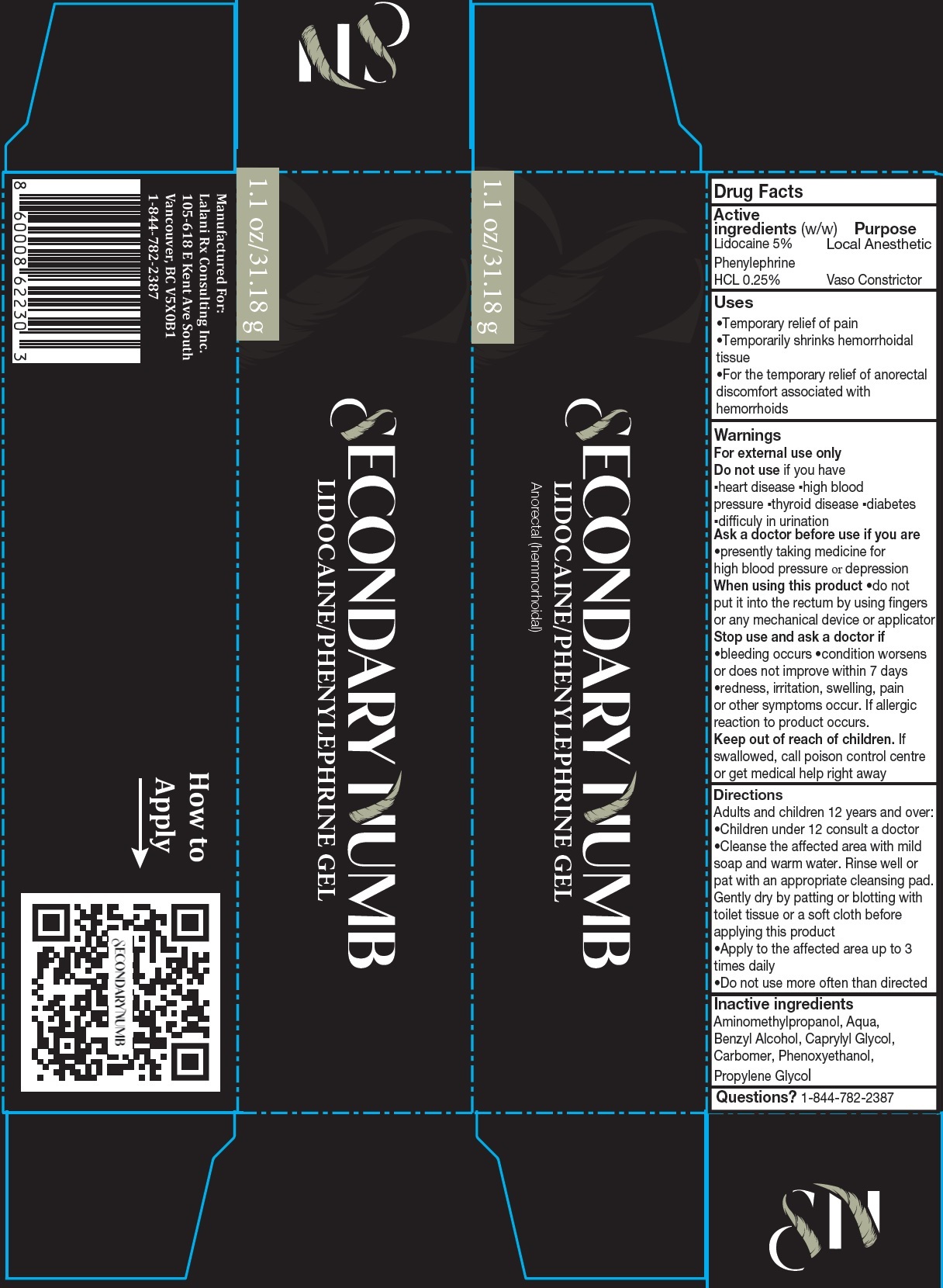 DRUG LABEL: SECONDARY NUMB Lidocaine Phenylephrine Gel
NDC: 83120-378 | Form: GEL
Manufacturer: LALANI Rx Consulting, Inc.
Category: otc | Type: HUMAN OTC DRUG LABEL
Date: 20231106

ACTIVE INGREDIENTS: LIDOCAINE 50 mg/1 g; PHENYLEPHRINE HYDROCHLORIDE 2.5 mg/1 g
INACTIVE INGREDIENTS: AMINOMETHYLPROPANOL; WATER; BENZYL ALCOHOL; CAPRYLYL GLYCOL; CARBOMER HOMOPOLYMER, UNSPECIFIED TYPE; PHENOXYETHANOL; PROPYLENE GLYCOL

SECONDARY NUMB Lidocaine/Phenylephrine Gel

Active ingredients (w/w)

Lidocaine 5% Phenylephrine HCL 0.25%

Purpose

Local Anesthetic

Vaso Constrictor

Uses

• Temporary relief of pain • Temporarily shrinks hemorrhoidal tissue • For the temporary relief of anorectal discomfort associated with hemorrhoids

Warnings

For external use only

Do not use

if you have ▪ heart disease ▪ high blood pressure ▪ thyroid disease ▪ diabetes ▪ difficuly in urination

Ask a doctor before use if you are

• presently taking medicine for high blood pressure or depression

When using this product

• do not put it into the rectum by using fingers or any mechanical device or applicator

Stop use and ask a doctor if

• bleeding occurs • condition worsens or does not improve within 7 days • redness, irritation, swelling, pain or other symptoms occur. If allergic reaction to product occurs.

Keep out of reach of children.

If swallowed, call poison control centre or get medical help right away

Directions

Adults and children 12 years and over: • Children under 12 consult a doctor • Cleanse the affected area with mild soap and warm water. Rinse well or pat with an appropriate cleansing pad. Gently dry by patting or blotting with toilet tissue or a soft cloth before applying this product • Apply to the affected area up to 3 times daily • Do not use more often than directed

Inactive ingredients

Aminomethylpropanol, Aqua, Benzyl Alcohol, Caprylyl Glycol, Carbomer, Phenoxyethanol, Propylene Glycol

Questions?

1-844-782-2387